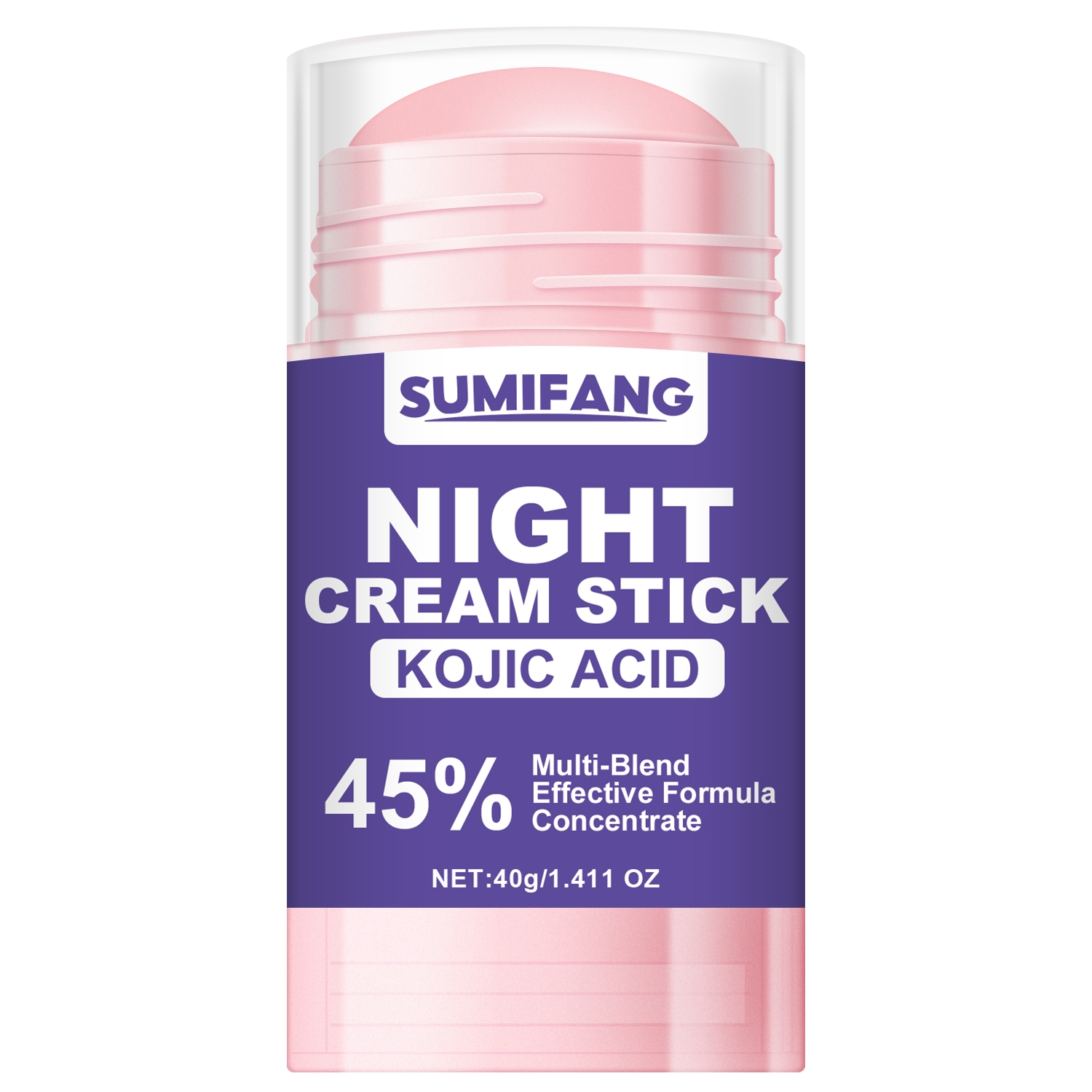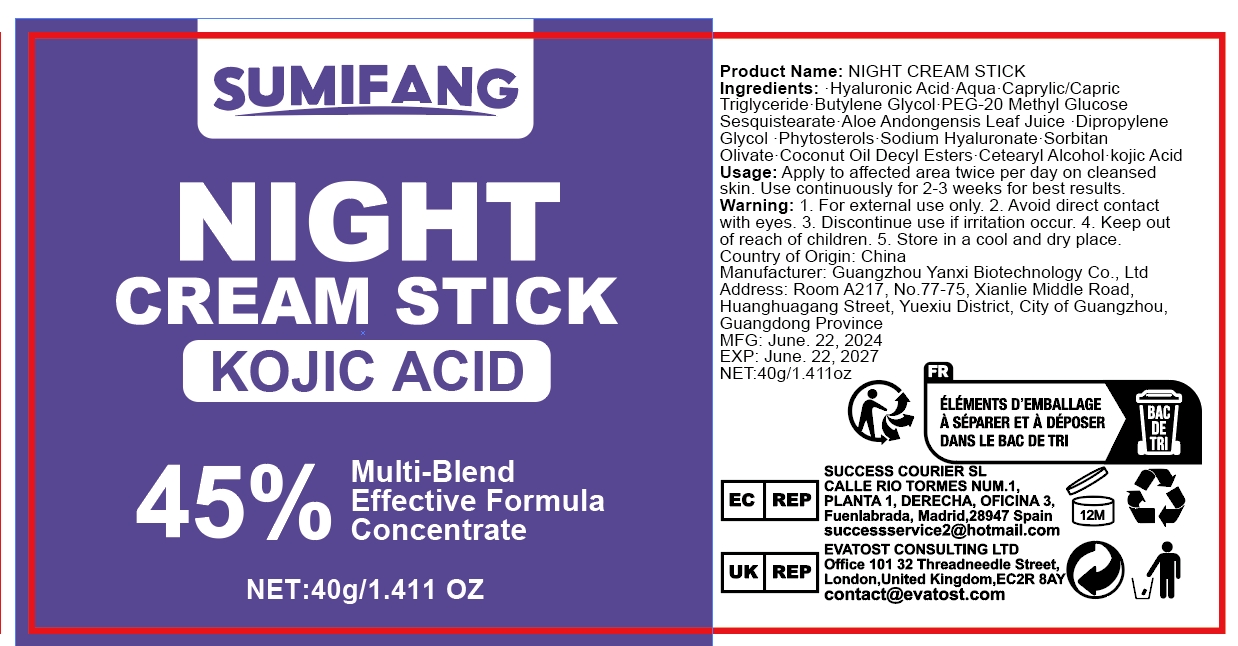 DRUG LABEL: KOJIC ACID Cream
NDC: 84025-095 | Form: CREAM
Manufacturer: Guangzhou Yanxi Biotechnology Co.. Ltd
Category: otc | Type: HUMAN OTC DRUG LABEL
Date: 20240729

ACTIVE INGREDIENTS: KOJIC ACID 5 mg/40 g; MINERAL OIL 3 mg/40 g
INACTIVE INGREDIENTS: WATER

DOSAGE AND ADMINISTRATION

Cream sticks for daily skin care

WARNINGS

Keep out of children

INACTIVE INGREDIENT

Aqua

INDICATIONS AND USAGE

Suitable for dull and rough skin

keep out of children

PURPOSE

Brightens and moisturizes the skin